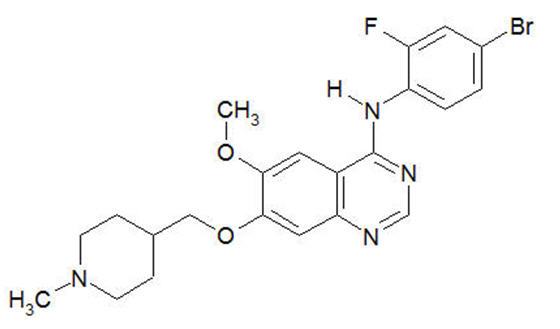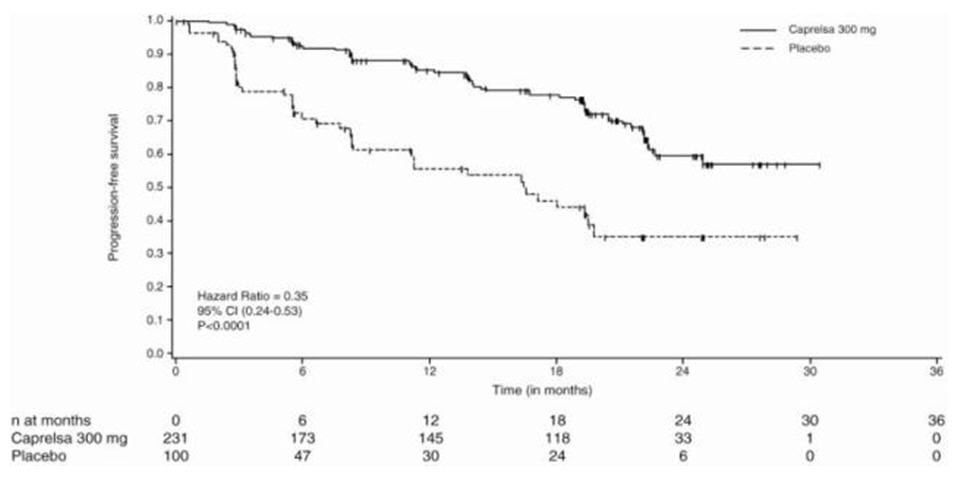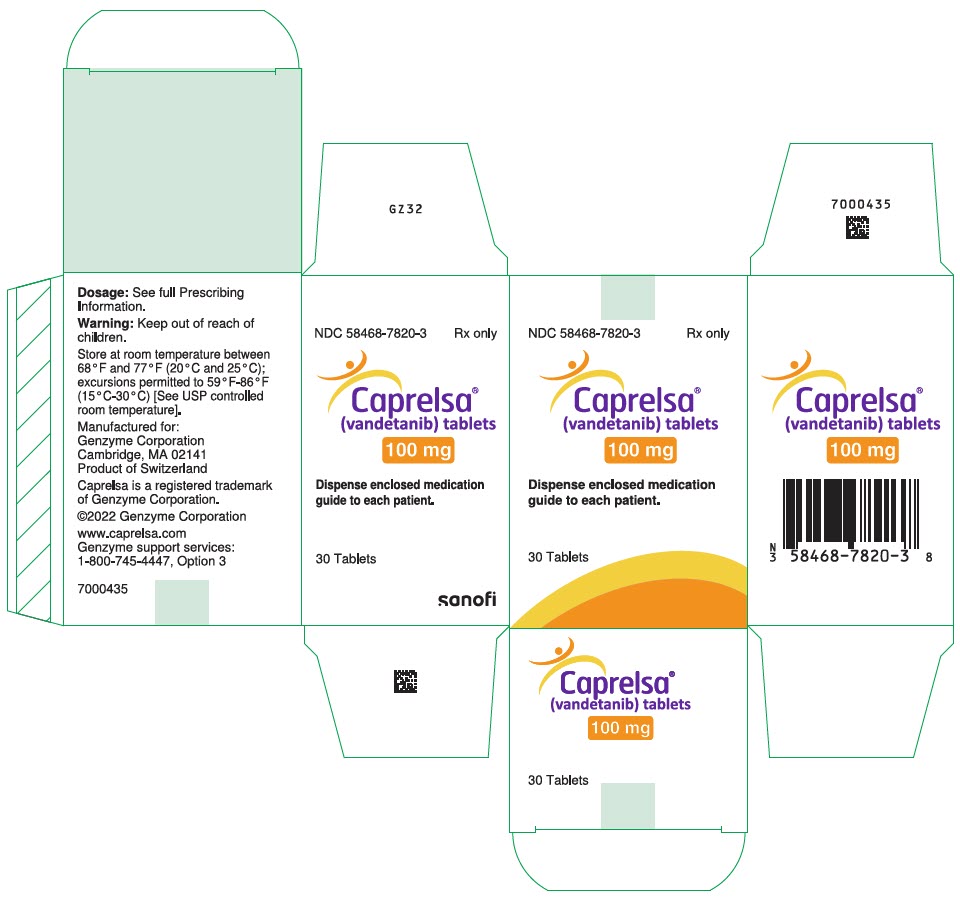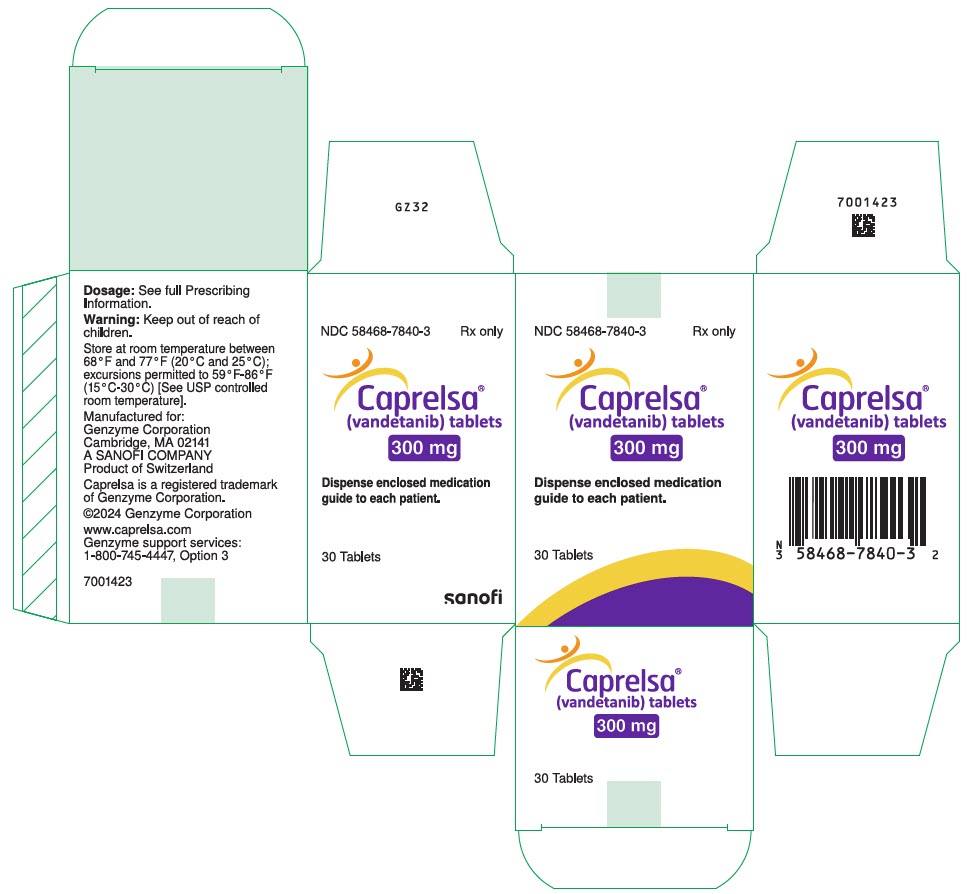 DRUG LABEL: CAPRELSA
NDC: 58468-7820 | Form: TABLET, FILM COATED
Manufacturer: Genzyme Corporation
Category: prescription | Type: HUMAN PRESCRIPTION DRUG LABEL
Date: 20260202

ACTIVE INGREDIENTS: VANDETANIB 100 mg/1 1
INACTIVE INGREDIENTS: DIBASIC CALCIUM PHOSPHATE DIHYDRATE; MICROCRYSTALLINE CELLULOSE; CROSPOVIDONE (120 .MU.M); POVIDONE, UNSPECIFIED; MAGNESIUM STEARATE; HYPROMELLOSE, UNSPECIFIED; TITANIUM DIOXIDE; POLYETHYLENE GLYCOL 300

HIGHLIGHTS OF PRESCRIBING INFORMATION

These highlights do not include all the information needed to use CAPRELSA safely and effectively. See full prescribing information for CAPRELSA.
CAPRELSA® (vandetanib) tablets, for oral use
Initial U.S. Approval: 2011

WARNING: QT PROLONGATION, TORSADES DE POINTES, AND SUDDEN DEATH

See full prescribing information for complete boxed warning.

CAPRELSA can prolong the QT interval. Torsades de pointes and sudden death have occurred in patients receiving CAPRELSA. Do not use CAPRELSA in patients with hypocalcemia, hypokalemia, hypomagnesemia, or long QT syndrome. Correct hypocalcemia, hypokalemia and/or hypomagnesemia prior to CAPRELSA administration. Monitor electrolytes periodically. Avoid drugs known to prolong the QT interval (5.1).

RECENT MAJOR CHANGES

Warnings and Precautions (5.16) | 05/2025

1 INDICATIONS AND USAGE

CAPRELSA is a kinase inhibitor indicated for the treatment of symptomatic or progressive medullary thyroid cancer in patients with unresectable locally advanced or metastatic disease. (1)

Use CAPRELSA in patients with indolent, asymptomatic or slowly progressing disease only after careful consideration of the treatment related risks of CAPRELSA. (1)

2 DOSAGE AND ADMINISTRATION

- 300 mg once daily. (2)
- CAPRELSA may be taken with or without food. (2)
- Dosage reduction may be necessary in the event of severe toxicities or QTc interval prolongation. (2.1)
- The starting dose is 200 mg in patients with moderate renal impairment. (2.1)

3 DOSAGE FORMS AND STRENGTHS

100 mg and 300 mg tablets (3)

4 CONTRAINDICATIONS

Do not use in patients with congenital long QT syndrome. (4)

5 WARNINGS AND PRECAUTIONS

- Prolonged QT interval, torsades de pointes, and sudden death: Monitor electrocardiograms and levels of serum potassium, calcium, magnesium and TSH. Reduce CAPRELSA dose as appropriate. (2.1, 5.1)
- Severe skin reactions, including toxic epidermal necrolysis and Stevens-Johnson syndrome, some fatal. Discontinue CAPRELSA for severe skin reactions. (2.1, 5.2)
- Interstitial lung disease (ILD), including fatalities: investigate unexplained non-specific respiratory signs and symptoms. Discontinue CAPRELSA for confirmed ILD. (2.1, 5.3)
- Ischemic cerebrovascular events, hemorrhage, heart failure, diarrhea, hypertension, and reversible posterior leukoencephalopathy syndrome: Discontinue or interrupt CAPRELSA. (2.1, 5.4, 5.5, 5.6, 5.7, 5.9, 5.10)
- Impaired wound healing: Withhold for at least 1 month prior to elective surgery. Do not administer CAPRELSA for at least 2 weeks following major surgery and until adequate wound healing. The safety of resumption of treatment with CAPRELSA after resolution of wound healing complications has not been established. (5.14)
- Embryo-fetal toxicity: Can cause fetal harm. Advise women of reproductive potential of the potential risk to a fetus and to use effective contraception. (5.15, 8.1)
- Osteonecrosis, including osteonecrosis of the jaw: Withhold CAPRELSA for 1 month prior to scheduled dental surgery and permanently discontinue if osteonecrosis occurs (5.16, 6.2).

6 ADVERSE REACTIONS

The most common adverse drug reactions (>20%) seen with CAPRELSA and with a between-arm difference of ≥5 % have been diarrhea/colitis, rash, acneiform dermatitis, hypertension, nausea, headache, upper respiratory tract infections, decreased appetite and abdominal pain. (6)

To report SUSPECTED ADVERSE REACTIONS, Contact Sanofi Genzyme at 1-800-633-1610 or FDA at 1-800-FDA-1088 or www.fda.gov/medwatch.

7 DRUG INTERACTIONS

- Avoid the use of strong CYP3A4 inducers because they may decrease CAPRELSA exposure. (7.1)
- Avoid the use of agents that prolong the QT interval. (5.11)

FULL PRESCRIBING INFORMATION

WARNING: QT PROLONGATION, TORSADES DE POINTES, AND SUDDEN DEATH

CAPRELSA can prolong the QT interval. Torsades de pointes and sudden death have occurred in patients receiving CAPRELSA. Do not use CAPRELSA in patients with hypocalcemia, hypokalemia, hypomagnesemia, or long QT syndrome. Correct hypocalcemia, hypokalemia and/or hypomagnesemia prior to CAPRELSA administration. Monitor electrolytes periodically. Avoid drugs known to prolong the QT interval [see Warnings and Precautions (5.1)].

1 INDICATIONS AND USAGE

CAPRELSA is indicated for the treatment of symptomatic or progressive medullary thyroid cancer in patients with unresectable locally advanced or metastatic disease.

Use CAPRELSA in patients with indolent, asymptomatic or slowly progressing disease only after careful consideration of the treatment related risks of CAPRELSA.

2 DOSAGE AND ADMINISTRATION

The recommended dose of CAPRELSA is 300 mg taken orally once daily until disease progression or unacceptable toxicity occurs.

CAPRELSA may be taken with or without food.

Do not take a missed dose within 12 hours of the next dose.

Do not crush CAPRELSA tablets. The tablets can be dispersed in 2 ounces of water by stirring for approximately 10 minutes (will not completely dissolve). Do not use other liquids for dispersion. Swallow immediately after dispersion. Mix any remaining residue with 4 additional ounces of water and swallow.

The dispersion can also be administered through nasogastric or gastrostomy tubes.

2.1 Dosage Adjustment

For Adverse Reactions

The 300 mg daily dose can be reduced to 200 mg (two 100 mg tablets) and then to 100 mg for Common Terminology Criteria for Adverse Events (CTCAE) Grade 3 or greater toxicities.

Interrupt CAPRELSA for the following:

- Corrected QT interval, Fridericia (QTcF) greater than 500 ms: Resume at a reduced dose when the QTcF returns to less than 450 ms.
- CTCAE Grade 3 or greater toxicity: Resume at a reduced dose when the toxicity resolves or improves to CTCAE Grade 1.

For recurrent toxicities, reduce the dose of CAPRELSA to 100 mg after resolution or improvement to CTCAE Grade 1 severity, if continued treatment is warranted.

Adverse events including QT interval prolongation should be monitored closely as they may not resolve fully until approximately three plasma half-lives of the drug. Monitor appropriately [see Warnings and Precautions (5.1), (5.2), (5.3), (5.4), (5.5), (5.6), (5.7), and (5.9)].

For Patients with Renal Impairment

Reduce the starting dose to 200 mg in patients with moderate (creatinine clearance ≥30 to <50 mL/min) renal impairment [see Warnings and Precautions (5.12) and Use in Specific Populations (8.6)].

For Patients with Hepatic Impairment

CAPRELSA is not recommended for use in patients with moderate and severe hepatic impairment [see Use in Specific Populations (8.7)].

3 DOSAGE FORMS AND STRENGTHS

CAPRELSA 100 mg tablets are white, round, biconvex, film-coated, and intagliated with 'Z 100' on one side and plain on the reverse side.

CAPRELSA 300 mg tablets are white, oval, biconvex, film-coated, and intagliated with 'Z 300' on one side and plain on the reverse side.

4 CONTRAINDICATIONS

Do not use in patients with congenital long QT syndrome [see Boxed Warning].

5 WARNINGS AND PRECAUTIONS

5.1 QT Prolongation and Torsades de Pointes

CAPRELSA can prolong the QT interval in a concentration-dependent manner [see Clinical Pharmacology (12.2)]. Torsades de pointes, ventricular tachycardia and sudden deaths have occurred in patients treated with CAPRELSA.

Do not start CAPRELSA treatment in patients whose QTcF interval is greater than 450 ms. Do not administer CAPRELSA to patients who have a history of Torsades de pointes, congenital long QT syndrome, bradyarrhythmias or uncompensated heart failure. CAPRELSA has not been studied in patients with ventricular arrhythmias or recent myocardial infarction. Vandetanib exposure is increased in patients with impaired renal function. Reduce the starting dose to 200 mg in patients with moderate renal impairment and monitor QT interval frequently.

Obtain an ECG and serum potassium, calcium, magnesium and TSH at baseline, 2 to 4 weeks and 8 to 12 weeks after starting treatment with CAPRELSA, and every 3 months thereafter. Monitor electrolytes and ECGs more frequently in patients who experience diarrhea. Following any dose reduction for QT prolongation or any dose interruption greater than 2 weeks, conduct QT assessments as described above. Maintain serum potassium levels of 4 mEq/L or higher (within normal range) and maintain serum magnesium and calcium levels within normal ranges to reduce the risk of QT prolongation.

Avoid using CAPRELSA with drugs known to prolong the QT interval [see Warnings and Precautions (5.11) and Drug Interactions (7.4)]. If such drugs are given to patients already receiving CAPRELSA and no alternative therapy exists, perform ECG monitoring of the QT interval more frequently.

Stop CAPRELSA in patients who develop a QTcF greater than 500 ms until the QTcF returns to less than 450 ms. Dosing of CAPRELSA can then be resumed at a reduced dose [see Dosage and Administration (2.1)].

5.2 Severe Skin Reactions

Severe and sometimes fatal skin reactions, including toxic epidermal necrolysis (TEN) and Stevens-Johnson syndrome, have occurred in patients treated with CAPRELSA. Permanently discontinue CAPRELSA for severe skin reactions and refer the patient for urgent medical evaluation. Systemic therapies such as corticosteroids may be required.

Photosensitivity reactions can occur during CAPRELSA treatment and up to 4 months after treatment discontinuation.

5.3 Interstitial Lung Disease

Interstitial Lung Disease (ILD) or pneumonitis, including fatalities, has occurred in patients treated with CAPRELSA. Consider a diagnosis of ILD in patients presenting with non-specific respiratory signs and symptoms.

Interrupt CAPRELSA for acute or worsening pulmonary symptoms. Discontinue CAPRELSA if ILD is confirmed.

5.4 Ischemic Cerebrovascular Events

Ischemic cerebrovascular events, including fatalities, occurred in patients treated with CAPRELSA. In the randomized medullary thyroid cancer (MTC) study, ischemic cerebrovascular events occurred more frequently with CAPRELSA compared to placebo (1.3% compared to 0%). The safety of resumption of CAPRELSA therapy after resolution of an ischemic cerebrovascular event has not been studied. Discontinue CAPRELSA in patients who experience a severe ischemic cerebrovascular event.

5.5 Hemorrhage

Serious hemorrhagic events, including fatalities, occurred in patients treated with CAPRELSA. Do not administer CAPRELSA to patients with a recent history of hemoptysis of ≥1/2 teaspoon of red blood. Discontinue CAPRELSA in patients with severe hemorrhage.

5.6 Heart Failure

Heart failure, including fatalities, occurred in patients treated with CAPRELSA. Monitor for signs and symptoms of heart failure. Consider discontinuation of CAPRELSA in patients with heart failure. Heart failure may not be reversible upon stopping CAPRELSA.

5.7 Diarrhea

Diarrhea of Grade 3 or greater severity occurred in 11% of patients receiving CAPRELSA in the randomized MTC study. If diarrhea occurs, carefully monitor serum electrolytes and ECGs to reduce the risk and enable early detection of QT prolongation resulting from dehydration [see Warnings and Precautions (5.1)]. Interrupt CAPRELSA for severe diarrhea. Upon improvement, resume CAPRELSA at a reduced dose [see Dosage and Administration (2.1)].

5.8 Hypothyroidism

In the randomized MTC study in which 90% of the patients enrolled had prior thyroidectomy, increased dosing of thyroid replacement therapy was required in 49% of CAPRELSA-treated patients compared to 17% of placebo-treated patients. Obtain Thyroid-stimulating hormone (TSH) at baseline, at 2 to 4 weeks and 8 to 12 weeks after starting treatment with CAPRELSA, and every 3 months thereafter. If signs or symptoms of hypothyroidism occur, examine thyroid hormone levels and adjust thyroid replacement therapy accordingly.

5.9 Hypertension

Hypertension, including hypertensive crisis, has occurred in patients treated with CAPRELSA. Monitor all patients for hypertension. Dose reduction or interruption for hypertension may be necessary. If hypertension cannot be controlled, do not resume CAPRELSA [see Dosage and Administration (2.1)].

5.10 Reversible Posterior Leukoencephalopathy Syndrome

Reversible posterior leukoencephalopathy syndrome (RPLS), a syndrome of subcortical vasogenic edema diagnosed by an MRI of the brain, has occurred in patients treated with CAPRELSA. Consider this syndrome in any patient presenting with seizures, headache, visual disturbances, confusion or altered mental function. In clinical studies, three of four patients who developed RPLS while taking CAPRELSA also had hypertension. Discontinue CAPRELSA treatment in patients with RPLS.

5.11 Drug Interactions

Avoid administration of CAPRELSA with anti-arrhythmic drugs (including but not limited to amiodarone, disopyramide, procainamide, sotalol, dofetilide) and other drugs that may prolong the QT interval (including but not limited to chloroquine, clarithromycin, dolasetron, granisetron, haloperidol, methadone, moxifloxacin, and pimozide) [see Drug Interactions (7.4) and Clinical Pharmacology (12.2)].

5.12 Renal Failure

Renal failure occurred in patients treated with CAPRELSA [see Adverse Reactions (6.1)]. Withhold, reduce the dose or permanently discontinue based on severity [see Dosage and Administration (2.1)].

Vandetanib exposure is increased in patients with impaired renal function. Reduce the starting dose to 200 mg in patients with moderate renal impairment and monitor the QT interval closely [see Dosage and Administration (2.1)]. Vandetanib is not recommended for use in patients with severe renal impairment (clearance below 30 mL/min). There is no information available for patients with end-stage renal disease requiring dialysis [see Boxed Warning, Dosage and Administration (2.1), Use in Specific Populations (8.6) and Clinical Pharmacology (12.3)].

5.13 Hepatic Impairment

CAPRELSA is not recommended for use in patients with moderate and severe hepatic impairment, as safety and efficacy have not been established [see Dosage and Administration (2.1)].

5.14 Impaired Wound Healing

Impaired wound healing can occur in patients who receive drugs that inhibit the VEGF signaling pathway. Impaired wound healing has occurred in patients treated with CAPRELSA.

Withhold CAPRELSA for at least 1 month prior to elective surgery. Do not administer CAPRELSA for at least 2 weeks following major surgery and until adequate wound healing. The safety of resumption of treatment with CAPRELSA after resolution of wound healing complications has not been established.

5.15 Embryo-Fetal Toxicity

Based on its mechanism of action and findings in animals, CAPRELSA can cause fetal harm when administered to a pregnant woman. In rats, vandetanib was embryotoxic, fetotoxic, and induced fetal malformations at exposures equivalent to or lower than those expected at the 300 mg clinical dose and had adverse effects on female fertility, embryofetal development, and postnatal development of pups.

Advise patients of the potential risk to a fetus. Advise females of reproductive potential to use effective contraception during treatment with CAPRELSA and for 4 months after the last dose. Advise males with female partners of reproductive potential to use effective contraception during treatment with CAPRELSA and for 4 months after the last dose [see Use in Specific Populations (8.1), (8.3)].

5.16 Osteonecrosis

Osteonecrosis, including osteonecrosis of the jaw (ONJ), has occurred during treatment with CAPRELSA. Concomitant exposure to other risk factors, such as bisphosphonates, denosumab, dental disease or invasive dental procedures, may increase the risk of ONJ. Perform an oral examination prior to and periodically during treatment with CAPRELSA. Advise patients regarding good oral hygiene practices. Avoid invasive dental procedures while on CAPRELSA treatment, particularly in patients at higher risk. Withhold CAPRELSA for at least one month prior to scheduled dental surgery or invasive dental procedures. Permanently discontinue CAPRELSA if ONJ develops. [see Adverse Reactions (6.2)].

6 ADVERSE REACTIONS

The following serious adverse reactions are discussed elsewhere in the label:

- QT Prolongation and Torsades de Pointes [see Boxed Warning, Warnings and Precautions (5.1)]
- Severe Skin Reactions [see Warnings and Precautions (5.2)]
- Interstitial Lung Disease [see Warnings and Precautions (5.3)]
- Ischemic Cerebrovascular Events [see Warnings and Precautions (5.4)]
- Hemorrhage [see Warnings and Precautions (5.5)]
- Heart Failure [see Warnings and Precautions (5.6)]
- Diarrhea [see Warnings and Precautions (5.7)]
- Hypothyroidism [see Warnings and Precautions (5.8)]
- Hypertension [see Warnings and Precautions (5.9)]
- Reversible Posterior Leukoencephalopathy Syndrome [see Warnings and Precautions (5.10)]
- Renal Failure [see Warnings and Precautions (5.12)]
- Embryo-Fetal Toxicity [see Warnings and Precautions (5.15)]
- Osteonecrosis [see Warnings and Precautions (5.16)]

6.1 Clinical Trials Experience

Because clinical trials are conducted under widely varying conditions, adverse reaction rates observed in the clinical trials of a drug cannot be directly compared to rates in the clinical trials of another drug and may not reflect the rates observed in practice.

Patients with unresectable locally advanced or metastatic medullary thyroid cancer were treated with CAPRELSA 300 mg (n=231) or Placebo (n=99). The population exposed to CAPRELSA was 58% male, 94% white, and had a median age of 50 years. The data described below reflect a median exposure to CAPRELSA for 607 days.

The most commonly reported adverse drug reactions which occurred in >20% of CAPRELSA-treated patients and with a between-arm difference of ≥5% included, in order of decreasing frequency: diarrhea/colitis, rash, acneiform dermatitis, hypertension, nausea, headache, upper respiratory tract infection, decreased appetite, and abdominal pain.

Among CAPRELSA-treated patients, dose interruption occurred in 109 (47%) and dose reduction occurred in 83 (36%). Adverse reactions led to study treatment discontinuation in 28 of 231 patients (12%) receiving CAPRELSA and in 3 of 99 patients (3.0%) receiving placebo. Adverse reactions leading to permanent discontinuation in 2 or more (≥0.9%) patients treated with CAPRELSA were: asthenia (1.7%), rash (1.7%), diarrhea (0.9%), fatigue (0.9%), pyrexia (0.9%), elevated creatinine (0.9%), QT prolongation (0.9%), and hypertension (0.9%).

Table 1: Per-Patient Incidence of Selected Adverse Reactions Occurring at a Higher Incidence in CAPRELSA-Treated Patients During Randomized Treatment (Between-Arm Difference of ≥5% [All Grades] [CTCAE version 3 was used to grade adverse events.])
System Organ Class | CAPRELSA 300 mg |  | Placebo
Preferred Term | N=231 |  | N=99
 | All Grades (%) | Grade 3 or 4 (%) | All Grades (%) | Grade 3 or 4 (%)
Gastrointestinal Disorders
Diarrhea/Colitis | 57 | 11 | 27 | 2
Nausea | 33 | 1 | 16 | 0
Abdominal Pain [Includes abdominal pain, abdominal pain upper, lower abdominal pain, and abdominal discomfort.] | 21 | 3 | 11 | 0
Vomiting | 15 | 1 | 7 | 0
Dyspepsia | 11 | 0 | 4 | 0
Dry Mouth | 9 | 0 | 3 | 0
Skin and Cutaneous Disorders
Rash [Includes rash, rash (erythematous, generalized, macular, maculopapular, papular, pruritic, and exfoliative), dermatitis, dermatitis bullous, generalized erythema, and eczema.] | 53 | 5 | 12 | 0
Dermatitis Acneiform/Acne | 35 | 1 | 7 | 0
Dry Skin | 15 | 0 | 5 | 0
Photosensitivity Reaction | 13 | 2 | 0 | 0
Pruritus | 11 | 1 | 4 | 0
Nail abnormalities [Includes nail disorder, nail bed inflammation, nail bed tenderness, paronychia, nail bed infection, and nail infection.] | 9 | 0 | 0 | 0
Alopecia | 8 | N/A | 0 | N/A
Vascular Disorders
Hypertension/Hypertensive Crisis/Accelerated Hypertension | 33 | 9 | 5 | 1
Nervous System Disorders
Headache | 26 | 1 | 9 | 0
Dysgeusia | 8 | 0 | 3 | 0
General Disorders
Fatigue [Included in Table 1 due to the increased incidence of severe fatigue in the CAPRELSA group compared to the placebo group.] | 24 | 6 | 23 | 1
Infections
Upper Respiratory Tract Infections [Includes laryngitis, nasopharyngitis, pharyngitis, sinusitis, upper respiratory tract infection, acute sinusitis, rhinitis, and tracheitis.] | 23 | 0 | 16 | 0
Metabolic and Nutritional Disorders
Decreased Appetite | 21 | 4 | 12 | 0
Hypocalcemia | 11 | 2 | 3 | 0
Investigations
ECG QT Prolonged [69% had QT prolongation >450 ms and 7% had QT prolongation >500 ms by ECG using Fridericia correction.] | 14 | 8 | 1 | 1
Eye Disorders
Corneal Abnormalities [Includes corneal edema, corneal opacity, corneal dystrophy, corneal pigmentation, keratopathy, arcus lipoides, corneal deposits, and acquired corneal dystrophy.] | 13 | 0 | 1 | 0
Blurred Vision | 9 | 0 | 1 | 0
Renal Disorders
Proteinuria | 10 | 0 | 2 | 0
Psychiatric Disorders
Depression | 10 | 2 | 3 | 0
Endocrine Disorders
Hypothyroidism | 6 | 0 | 0 | 0
Musculoskeletal Disorders
Muscle Spasms | 6 | 0 | 1 | 0

Other Clinically Relevant Adverse Effects

In patients with medullary thyroid cancer treated with CAPRELSA or placebo (NCT00410761), clinically important uncommon adverse drug reactions included pancreatitis (0.4% vs 0%), intestinal perforation (0.4% vs 0%), and heart failure (0.9% vs 0%).

Blurred vision was commonly reported (9% vs 1%) in this trial. Scheduled slit lamp examinations revealed corneal opacities (vortex keratopathies) in treated patients, which can lead to halos and decreased visual acuity. Perform ophthalmologic examination, including slit lamp examination, in patients who report visual changes.

Grade 1 to 2 bleeding events were also more common in patients receiving CAPRELSA compared to placebo (14% vs 7%).

Table 2: Per-Patient Incidence of Selected Laboratory Abnormalities in Patients with MTC Occurring at a Higher Incidence in CAPRELSA-Treated Patients (Between-Arm Difference of ≥5% [All Grades] [CTCAE version 3 was used to grade laboratory abnormalities.])
Laboratory Abnormalities | CAPRELSA 300 mg N=231 |  | Placebo N=99
 | All Grades (%) | Grade 3 or 4 (%) | All Grades (%) | Grade 3 or 4 (%)
Chemistries
Hypocalcemia | 57 | 6 | 25 | 3
ALT Increased | 51 | 2 | 19 | 0
Hypoglycemia | 24 | 0 | 7 | 1
Creatinine Increased | 16 | 0 | 1 | 0
Hypomagnesemia | 7 | <1 | 2 | 0
Hematologic
Neutropenia | 10 | <1 | 5 | 2
Thrombocytopenia | 9 | 0 | 3 | 0

No patient with a Grade 3 to 4 ALT elevation had a concomitant increase in bilirubin in the MTC study.

6.2 Postmarketing Experience

The following adverse reactions have been identified during post-approval use of CAPRELSA. Because these reactions are reported voluntarily from a population of uncertain size, it is not always possible to reliably estimate their frequency or establish a causal relationship to drug exposure.

Vascular disorders: Arterial (including aortic) aneurysms, dissections, and rupture

Musculoskeletal and connective tissue disorders: Osteonecrosis

General disorders: Impaired wound healing

7 DRUG INTERACTIONS

7.1 Effect of CYP3A4 Inducers on CAPRELSA

Rifampicin, a strong CYP3A4 inducer, decreased vandetanib plasma concentrations. Avoid concomitant use of known strong CYP3A4 inducers during CAPRELSA therapy. Avoid concomitant use of St. John's wort because it can decrease vandetanib exposure unpredictably [see Clinical Pharmacology (12.3)].

7.2 Effect of CAPRELSA on OCT2 Transporter

CAPRELSA increased plasma concentrations of metformin that is transported by the organic cation transporter type 2 (OCT2). Use caution and closely monitor for toxicities when administering CAPRELSA with drugs that are transported by OCT2 [see Clinical Pharmacology (12.3)].

7.3 Effect of CAPRELSA on Digoxin

CAPRELSA increased plasma concentrations of digoxin. Use caution and closely monitor for toxicities when administering CAPRELSA with digoxin [see Clinical Pharmacology (12.3)].

7.4 Drugs that Prolong the QT Interval

Avoid concomitant use of CAPRELSA with agents that may prolong the QT interval [see Warnings and Precautions (5.11)].

8 USE IN SPECIFIC POPULATIONS

8.1 Pregnancy

Risk Summary

Based on its mechanism of action and findings in animals, CAPRELSA can cause fetal harm when administered to a pregnant woman. There are no available human data on CAPRELSA use in pregnant women to inform a drug-associated risk. Vandetanib is embryotoxic, fetotoxic, and induced fetal malformations in rats at exposures less than or equal to those expected at the recommended human dose of 300 mg/day. Advise patients of the potential risk to a fetus.

In the U.S. general population, the estimated background risk of major birth defects and miscarriage in clinically recognized pregnancies is 2% to 4% and 15% to 20%, respectively.

Data

Animal data

In reproductive toxicity studies, administration of vandetanib to female rats prior to mating and through the first week of pregnancy at a dose of 25 mg/kg/day (approximately equal to the human exposure at the 300 mg clinical dose based on Cmax), there were increases in pre-implantation loss and post-implantation loss resulting in a reduction in the number of live embryos.

During organogenesis, vandetanib caused an increase in post-implantation loss, including occasional total litter loss at a dose of 25 mg/kg/day. At doses greater than 10 mg/kg/day (approximately 0.4 times the human Cmax at the 300 mg clinical dose) treatment with vandetanib resulted in increases in late embryofetal death and decreases in fetal birth weight. A no-effect level for malformations was not identified in this study. Administration of vandetanib at doses greater than or equal to 1 mg/kg/day (approximately 0.03 times the human Cmax at the 300 mg clinical dose) resulted in dose dependent increases in both malformations of the heart vessels and skeletal variations including delayed ossification of the skull, vertebrae, and sternum, indicating delayed fetal development.

In a rat prenatal and postnatal development study, at doses (1 and 10 mg/kg/day) producing mild maternal toxicity during gestation and/or lactation, vandetanib decreased pup survival and reduced postnatal pup growth. Reduced postnatal pup growth was associated with a delay in physical development.

8.2 Lactation

Risk Summary

There are no data on the presence of vandetanib or its metabolites in human milk, the effects on the breastfed child or on milk production. Vandetanib was present in the milk of lactating rats (see Data). Because of the potential for serious adverse reactions from CAPRELSA in breastfed children, advise lactating women not to breastfeed during treatment with CAPRELSA and for 4 months after the last dose.

Data

Animal data

In nonclinical studies, vandetanib was excreted in rat milk and found in plasma of pups following dosing to lactating rats. Vandetanib transfer in breast milk resulted in relatively constant exposure in pups due to the long half-life of the drug.

8.3 Females and Males of Reproductive Potential

Pregnancy Testing

Verify the pregnancy status of females of reproductive potential prior to initiating treatment with CAPRELSA [see Use in Specific Populations (8.1)].

Contraception

CAPRELSA can cause fetal harm when administered to a pregnant woman [see Use in Specific Populations (8.1)].

Females

Advise females of reproductive potential to use effective contraception during treatment with CAPRELSA and for 4 months after the last dose.

Males

Advise males with female partners of reproductive potential to use effective contraception during treatment with CAPRELSA and for 4 months after the last dose.

Infertility

There are no data on the effect of CAPRELSA on human fertility. Results from animal studies indicate that vandetanib can impair male and female fertility [see Nonclinical Toxicology (13.1)].

8.4 Pediatric Use

Safety and efficacy of CAPRELSA in pediatric patients have not been established.

8.5 Geriatric Use

The MTC study of CAPRELSA did not include sufficient numbers of patients aged 65 years and over to determine whether they respond differently compared to younger patients.

8.6 Renal Impairment

Vandetanib exposure is increased in patients with impaired renal function. Reduce the starting dose to 200 mg in patients with moderate (creatinine clearance ≥30 to <50 mL/min) renal impairment [see Dosage and Administration (2.1), Warnings and Precautions (5.12), and Clinical Pharmacology (12.3)].

Vandetanib is not recommended for use in patients with severe renal impairment (clearance below 30 mL/min) [see Warnings and Precautions (5.12)]. Patients with end-stage renal disease requiring dialysis were not studied [see Adverse Reactions (6.1)].

8.7 Hepatic Impairment

The pharmacokinetics of CAPRELSA were evaluated after a single dose of 800 mg in subjects with mild (n=8), moderate (n=7), and severe (n=6) hepatic impairment and normal hepatic function (n=5). Subjects with mild (Child-Pugh class A), moderate (Child-Pugh class B), and severe (Child-Pugh class C) hepatic impairment had comparable mean AUC and clearance values to those with normal hepatic function.

There are limited data in patients with liver impairment (serum bilirubin greater than 1.5 times the upper limit of normal). CAPRELSA is not recommended for use in patients with moderate and severe hepatic impairment, as safety and efficacy have not been established [see Dosage and Administration (2.1) and Warnings and Precautions (5.13)].

10 OVERDOSAGE

In the event of an overdose, monitor patients closely for QTc prolongation. Adverse events including QT interval prolongation should be monitored closely as they may not resolve fully until approximately three plasma half-lives of the drug.

11 DESCRIPTION

Vandetanib has the chemical name N-(4-bromo-2-fluorophenyl)-6-methoxy-7-[(1-methylpiperidin-4-yl) methoxy]quinazolin-4-amine.

The structural and molecular formulas are:

C22H24BrFN4O2

Vandetanib has a molecular weight of 475.36 g/mol. Vandetanib exhibits pH-dependent solubility, with increased solubility at lower pH. Vandetanib is practically insoluble in water with a value of 0.008 mg/mL at 25°C (77°F).

CAPRELSA tablets for daily oral administration are available in two dosage strengths containing either 100 mg or 300 mg of vandetanib. The tablet cores contain the following inactive ingredients: calcium hydrogen phosphate dihydrate, crospovidone, magnesium stearate, microcrystalline cellulose, and povidone. The tablet film-coat contains the following inactive ingredients: hypromellose 2910, macrogol 300, and titanium dioxide E171.

12 CLINICAL PHARMACOLOGY

12.1 Mechanism of Action

In vitro studies have shown that vandetanib inhibits the tyrosine kinase activity of the EGFR and VEGFR families, RET, BRK, TIE2, and members of the EPH receptor and Src kinase families. These receptor tyrosine kinases are involved in both normal cellular function and pathologic processes such as oncogenesis, metastasis, tumor angiogenesis, and maintenance of the tumor microenvironment. In addition, the N-desmethyl metabolite of the drug, representing 7 to 17.1% of vandetanib exposure, has similar inhibitory activity to the parent compound for VEGF receptors (KDR and Flt-1) and EGFR.

In vitro, vandetanib inhibited epidermal growth factor (EGF)-stimulated receptor tyrosine kinase phosphorylation in tumor cells and endothelial cells and VEGF-stimulated tyrosine kinase phosphorylation in endothelial cells.

In vivo, vandetanib administration reduced tumor cell-induced angiogenesis, tumor vessel permeability, and inhibited tumor growth and metastasis in mouse models of cancer.

12.2 Pharmacodynamics

Cardiac Electrophysiology

In 231 patients with medullary thyroid cancer randomized to receive CAPRELSA 300 mg once daily in the phase 3 clinical trial. CAPRELSA was associated with sustained plasma concentration-dependent QT prolongation. Based on the exposure-response relationship, the mean (90% CI) QTcF change from baseline (ΔQTcF) was 35 (33–36) ms for the 300 mg dose. The ΔQTcF remained above 30 ms for the duration of the trial (up to 2 years). In addition, 36% of patients experienced greater than 60 ms increase in ΔQTcF and 4.3% of patients had QTcF greater than 500 ms. Cases of Torsades de pointes and sudden death have occurred [see Boxed Warning and Warnings and Precautions (5.1), (5.11)].

12.3 Pharmacokinetics

A population pharmacokinetic analysis of CAPRELSA was conducted in 231 patients with MTC following oral administration of 300 mg daily doses. The pharmacokinetics of CAPRELSA at the 300 mg dose in MTC patients are characterized by a mean clearance of approximately 13.2 L/h, a mean volume of distribution of approximately 7450 L, and a median plasma half-life of 19 days.

Absorption

Following oral administration of CAPRELSA, absorption is slow with peak plasma concentrations typically achieved at a median of 6 hours, range 4 to 10 hours, after dosing. Vandetanib accumulates approximately 8-fold on multiple dosing with steady state achieved in approximately 3 months.

Exposure to vandetanib is unaffected by food.

Distribution

Vandetanib binds to human serum albumin and α1-acid-glycoprotein with in vitro protein binding being approximately 90%. In ex vivo plasma samples from colorectal cancer patients at steady state exposure after 300 mg once daily, the mean percentage protein binding was 94%.

Metabolism

Following oral dosing of ^14C-vandetanib, unchanged vandetanib and metabolites vandetanib N-oxide and N-desmethyl vandetanib were detected in plasma, urine and feces. A glucuronide conjugate was seen as a minor metabolite in excreta only. N-desmethyl-vandetanib is primarily produced by CYP3A4 and vandetanib-N-oxide by flavin-containing monooxygenase enzymes FMO1 and FMO3. N-desmethyl-vandetanib and vandetanib-N-oxide circulate at concentrations of approximately 7–17% and 1.4–2.2%, respectively, of those of vandetanib.

Excretion

Within a 21-day collection period after a single dose of ^14C-vandetanib, approximately 69% was recovered with 44% in feces and 25% in urine. Excretion of the dose was slow and further excretion beyond 21 days would be expected based on the plasma half-life.

Vandetanib was not a substrate of hOCT2 expressed in HEK293 cells. Vandetanib inhibits the uptake of the selective OCT2 marker substrate ^14C-creatinine by HEK-OCT2 cells, with a mean IC50 of 2.1 μg/mL. This is higher than vandetanib plasma concentrations (0.81 μg/mL) observed after multiple dosing at 300 mg. Inhibition of renal excretion of creatinine by vandetanib provides an explanation for increases in plasma creatinine seen in human subjects receiving vandetanib.

Specific Populations

Effects of age and gender

In a population pharmacokinetic evaluation in cancer patients, no relationship was apparent between oral clearance of vandetanib and patient age or gender.

Ethnicity

Based on a cross-study comparison in a limited number of patients, Japanese (N=3) and Chinese (N=7) patients had average exposures of vandetanib that were higher than Caucasian (N=7) patients receiving the same dose of CAPRELSA.

Pediatric

The pharmacokinetics of vandetanib has not been evaluated in pediatric patients.

Effect of renal impairment

The pharmacokinetics of vandetanib were evaluated after a single CAPRELSA dose of 800 mg in six subjects with mild (creatinine clearance = 50 to <80 mL/min), eight subjects with moderate (creatinine clearance ≥30 to <50 mL/min), six subjects with severe (creatinine clearance <30 mL/min) renal impairment and ten subjects with normal (creatinine clearance >80 mL/min) renal function. Subjects with mild renal impairment had a comparable mean AUC of vandetanib to that with normal renal function. In subjects with moderate or severe renal impairment, the average AUC of vandetanib increased by 39% and 41%, respectively, compared to patients with normal renal function [see Dosage and Administration (2.1), Warnings and Precautions (5.12) and Use in Specific Populations (8.6)].

Drug Interactions

Effect of other drugs on CAPRELSA

Strong CYP3A4 inducers: In a cross-over study in 12 healthy volunteers, a single oral 300 mg dose of CAPRELSA was administered alone on day 1 and on day 10 in combination with daily doses of 600 mg of rifampicin (a strong CYP3A4 inducer) given on days 1 to 31. The coadministration of rifampicin with CAPRELSA decreased the geometric mean AUC0–504h of vandetanib by 40% (90% confidence interval (CI): 56%, 63%) compared to vandetanib alone. No clinically meaningful change in the mean Cmax of vandetanib was observed. The geometric mean AUC0–504h and Cmax of N-desmethylvandetanib increased by 266% and 414%, respectively, in the presence of rifampicin compared with vandetanib alone [see Drug Interactions (7.1)].

Strong CYP3A4 inhibitors: In a cross-over study in 14 healthy volunteers, a single oral 300 mg dose of CAPRELSA was administered alone and on day 4 in combination with daily doses of 200 mg of itraconazole (a strong CYP3A4 inhibitor) given on days 1 to 24. No change was observed in the geometric mean AUC0–504h or Cmax of vandetanib when itraconazole was coadministered with CAPRELSA.

Gastric pH elevating agents: In a cross-over study of 14 healthy volunteers, a single oral 300 mg dose of CAPRELSA was administered alone and in combination with five daily doses of 40 mg omeprazole (a proton pump inhibitor). No clinically meaningful change was observed in the geometric mean AUC0–504h and Cmax of vandetanib when omeprazole was coadministered with CAPRELSA.

In a cross-over study of 16 healthy volunteers, a single 300 mg oral dose of CAPRELSA was administered alone and after two oral doses of 150 mg of ranitidine (a H2 receptor antagonist) administered about 12 hours apart. No change was observed in the geometric mean AUC0–504h and Cmax of vandetanib when ranitidine was coadministered with CAPRELSA.

Effect of CAPRELSA on other drugs

Sensitive CYP3A4 substrates: In a cross-over study of 16 healthy volunteers, a single oral 7.5 mg dose of midazolam (as 2 mg/mL oral syrup), a sensitive CYP3A4 substrate, was administered alone and 8 days after receiving a single 800 mg oral dose of CAPRELSA. No change was observed in the geometric mean Cmax and AUCinf of midazolam when CAPRELSA was coadministered with midazolam.

Substrates of OCT2 transporter: In a cross-over study of 13 healthy volunteers, a single 1000 mg oral dose of metformin, a substrate of OCT2, was administered alone and 3 hours after receiving a single 800 mg oral dose of CAPRELSA. The coadministration of CAPRELSA with metformin increased the geometric mean AUCinf of metformin by 74% (90% CI: 58%, 92%) and geometric mean Cmax of metformin by 50% (90% CI: 34%, 67%) compared to metformin alone [see Drug Interactions (7.2)].

Substrates of P-glycoprotein transporter: In a cross-over study of 14 healthy volunteers, a single oral 0.25 mg dose of digoxin, a substrate of P-glycoprotein, was administered alone and in combination with a single 300 mg oral dose of CAPRELSA. The coadministration of CAPRELSA increased the geometric mean Cmax digoxin by 29% (90% CI: 10%, 52%) and the geometric mean of AUC0–t of digoxin by 23% (90% CI: 12%, 34%) compared to digoxin alone [see Drug Interactions (7.3)].

13 NONCLINICAL TOXICOLOGY

13.1 Carcinogenesis, Mutagenesis, Impairment of Fertility

Vandetanib was not carcinogenic in a 2-year study in rats when administered by daily oral gavage at doses of up to 10 mg/kg (0.7 times the human Cmax at the 300 mg clinical dose), or in the Tg∙RasH2 mouse when administered by daily oral gavage at doses of up to 30 mg/kg (~5 times the human Cmax at the clinical dose of 300 mg) for 26 weeks. Vandetanib was not mutagenic in vitro in the bacterial reverse mutation (Ames) assay and was not clastogenic in either the in vitro cytogenetic assay using human lymphocytes or in the in vivo rat micronucleus assay.

Based on nonclinical findings, male and female fertility may be impaired by treatment with CAPRELSA. In a fertility study of male rats, vandetanib had no effect on copulation or fertility rate when untreated females were mated with males administered 1, 5, or 20 mg/kg/day of vandetanib (approximately 0.03, 0.22, or 0.40 times, respectively, the human exposure based on area under the curve (AUC) in patients with cancer at the 300 mg clinical dose); however, in the same study there was a slight decrease in the number of live embryos in females mated with males treated at the 20 mg/kg/day dose level and an increase in preimplantation loss in females mated with males administered vandetanib at doses of ≥5 mg/kg/day. In a female fertility study, there was a trend towards increased estrus cycle irregularity, a slight reduction in pregnancy incidence and an increase in implantation loss. In a one-month repeat-dose toxicity study in rats, there was a decrease in the number of corpora lutea in the ovaries of rats administered 75 mg/kg/day vandetanib (approximately 1.8 times the human exposure based on AUC at the 300 mg clinical dose).

13.2 Animal Toxicology and/or Pharmacology

In an animal model of wound-healing, mice dosed with vandetanib had reduced skin-breaking strength compared with controls. This suggests that CAPRELSA slows but does not prevent wound healing. The appropriate interval between discontinuation of CAPRELSA and subsequent elective surgery required to avoid the risks of impaired wound healing has not been determined.

14 CLINICAL STUDIES

14.1 Clinical Trial in Patients with Medullary Thyroid Cancer

A double-blind, placebo-controlled study (Study D4200C00058, NCT00410761) randomized patients with unresectable locally advanced or metastatic medullary thyroid cancer to CAPRELSA 300 mg (n=231) versus placebo (n=100).

The major efficacy outcome measure was progression-free survival (PFS) with CAPRELSA compared to placebo. Other efficacy outcome measures included evaluation of overall survival (OS) and overall objective response rate (ORR). Centralized, independent blinded review of the imaging data was used in the assessment of PFS and ORR. Upon objective disease progression based on the investigator's assessment, patients were discontinued from blinded study treatment and given the option to receive open-label CAPRELSA. Forty-seven percent (109/231) of the patients initially randomized to CAPRELSA opted to receive open-label CAPRELSA after disease progression, and 79% (79/100) of the patients initially randomized to placebo opted to receive open-label CAPRELSA after disease progression.

The result of the PFS analysis, based on the central review RECIST assessment, showed a statistically significant improvement in PFS for patients randomized to CAPRELSA (Hazard Ratio (HR) = 0.35; 95% Confidence Interval (CI) = 0.24-0.53; p<0.0001). Analyses in the subgroups of patients who were symptomatic or had progressed within 6 months prior to their enrollment showed similar PFS results (HR = 0.31 95% CI: 0.19, 0.53 for symptomatic patients; HR = 0.41 95% CI: 0.25, 0.66 for patients who had progressed within 6 months prior to enrollment). Median final OS were similar across both treatment arms.

The overall objective response rate (ORR) for patients randomized to CAPRELSA was 44% compared to 1% for patients randomized to placebo. All objective responses were partial responses.

Figure 1: Kaplan-Meier Curves for Progression Free Survival in Study D4200C00058

Table 3: Efficacy Results in Study D4200C00058
 | Vandetanib 300 mg (N=231) | Placebo (N=100)
Progression Free Survival
Events (%) | 59 (26.0) | 41 (41.0)
Median, months | NR [Not reached] | 16.4
(95% CI) | (22.6, NE [Not estimable]) | (8.3, 19.7)
Hazard Ratio (95% CI) | 0.35 (0.24, 0.53)
p-value | <0.0001
Overall Survival
Deaths (%) | 116 (50.2) | 52 (52.0)
Median, months | 81.6 | 80.4
(95% CI) | (64.6, 98.5) | (52.5, NE)
Hazard Ratio (95% CI) | 0.99 (0.72, 1.38)
p-value | 0.975

15 REFERENCES

1. OSHA Hazardous Drugs (OSHA Technical Manual). OSHA.

16 HOW SUPPLIED/STORAGE AND HANDLING

100 mg Tablets available in bottles containing 30 tablets (NDC 58468-7820-3).

300 mg Tablets available in bottles containing 30 tablets (NDC 58468-7840-3).

16.1 Storage and Handling

CAPRELSA tablets should be stored at room temperature between 68°F and 77°F (20°C and 25°C); excursions permitted to 59°F–86°F (15°C-30°C) [See USP controlled room temperature].

Procedures for proper handling and disposal of anticancer drugs should be considered. A guideline on this subject has been published.^1 Do not crush CAPRELSA tablets.

17 PATIENT COUNSELING INFORMATION

Advise the patient to read the FDA-approved patient labeling (Medication Guide).

QT Prolongation and Torsades de Pointes

Advise patients to contact their healthcare provider in the event of syncope, pre-syncopal symptoms, and cardiac palpitations. Advise patients that their healthcare provider will monitor their electrolytes and ECGs during treatment [see Warnings and Precautions (5.1)].

Severe Skin Reactions

Advise patients to contact their healthcare provider in the event of skin reactions or rash [see Warnings and Precautions (5.2)].

Interstitial Lung Disease (ILD)

Advise patients to contact their health care provider in the event of sudden onset or worsening of breathlessness, persistent cough or fever [see Warnings and Precautions (5.3)].

Diarrhea

Advise patients to contact their healthcare provider in the event of diarrhea [see Warnings and Precautions (5.7)].

Reversible Posterior Leukoencephalopathy Syndrome (RPLS)

Advise patients to contact their healthcare provider in the event of seizures, headaches, visual disturbances, confusion or difficulty thinking [see Warnings and Precautions (5.10)].

Impaired Wound Healing

Advise patients that CAPRELSA may impair wound healing. Advise patients to inform their healthcare provider of any planned surgical procedure [see Warnings and Precautions (5.14)].

Osteonecrosis

Advise patients regarding good oral hygiene practices and to have preventive dentistry performed prior to treatment with CAPRELSA and throughout treatment with CAPRELSA and to inform their healthcare provider of any planned dental procedures.

Advise patients to immediately contact their healthcare provider for signs or symptoms associated with osteonecrosis [see Warnings and Precautions (5.16)].

Embryo-Fetal Toxicity

Advise females of reproductive potential of the potential risk to a fetus. Advise females to contact their healthcare provider if they become pregnant, or if pregnancy is suspected, during treatment with CAPRELSA [see Use in Specific Populations (8.1), (8.3)].

Advise females of reproductive potential to use effective contraception during treatment with CAPRELSA and for 4 months after the last dose [see Use in Specific Populations (8.3)].

Advise males with female partners of reproductive potential to use effective contraception during treatment with CAPRELSA and for 4 months after the last dose [see Use in Specific Populations (8.3)].

Lactation

Advise women not to breastfeed during treatment with CAPRELSA and for 4 months after the last dose [see Use in Specific Populations (8.2)].

Photosensitivity

Advise patients to use appropriate sun protection due to the increased susceptibility to sunburn while taking CAPRELSA and for at least 4 months after drug discontinuation [see Warnings and Precautions (5.2)].

Administration

Advise patients that CAPRELSA can be taken with or without food and not to crush CAPRELSA tablets [see Clinical Pharmacology (12.3)].

Manufactured for:
Genzyme Corporation
Cambridge, MA 02141
A SANOFI COMPANY

CAPRELSA is a registered trademark of Genzyme Corporation.
©2026 Genzyme Corporation.
For patent information: https://www.sanofi.us/en/products-and-resources/patents

MEDICATION GUIDE
CAPRELSA® (kap-rel-sah)
(vandetanib)
tablets

Read this Medication Guide before you start taking CAPRELSA and each time you get a refill. There may be new information. This Medication Guide does not take the place of talking to your healthcare provider about your medical condition or treatment.

What is the most important information I should know about CAPRELSA?
CAPRELSA can cause a change in the electrical activity of your heart called QT prolongation, which can cause irregular heartbeats and that may lead to death. You should not take CAPRELSA if you have had a condition called long QT syndrome since birth.
Your healthcare provider should perform tests to check the levels of your blood potassium, calcium, magnesium, and thyroid-stimulating hormone (TSH), as well as the electrical activity of your heart with a test called an electrocardiogram (ECG). You should have these tests:

- Before starting CAPRELSA
- Regularly during CAPRELSA treatment:
  - 2 to 4 weeks after starting CAPRELSA
  - 8 to 12 weeks after starting CAPRELSA
  - every 3 months thereafter
  - if your healthcare provider changes your dose of CAPRELSA
  - if you start taking medicine that causes QT prolongation
  - as instructed by your healthcare provider

Your healthcare provider may stop your CAPRELSA treatment for a while and restart you at a lower dose if you have QT prolongation.
Call your healthcare provider right away if you feel faint, light-headed, or feel your heart beating irregularly during treatment with CAPRELSA. These may be symptoms related to QT prolongation.
See "What are the possible side effects of CAPRELSA?" for more information about side effects.

What is CAPRELSA?
CAPRELSA is a prescription medicine used to treat medullary thyroid cancer that cannot be removed by surgery or that has spread to other parts of the body. It takes a long time to get rid of CAPRELSA from your body and you may be at risk for side effects related to CAPRELSA after you have stopped your treatment.
It is not known if CAPRELSA is safe and effective in children.

Who should not take CAPRELSA?
Do not take CAPRELSA if you have QT prolongation.

Before you take CAPRELSA, tell your healthcare provider about all of your medical conditions, including if you:

- have any heart problems, including a condition called congenital long QT syndrome
- have an irregular heartbeat
- take or have stopped taking a medicine that causes QT prolongation
- have low blood levels of potassium, calcium, or magnesium
- have high blood levels of thyroid-stimulating hormone
- have high blood pressure
- have skin problems
- have a history of breathing problems
- have a recent history of coughing up blood or bleeding
- have diarrhea
- have liver problems
- have kidney problems
- have seizures or are being treated for seizures
- have weak or soft bone problems (osteonecrosis), including osteonecrosis of the jaw
- plan to have any surgery, a dental procedure or have had a recent surgery. You should stop taking CAPRELSA at least 1 month before a planned surgery or dental procedure. See "What are the possible side effects of CAPRELSA?"
- are pregnant or plan to become pregnant. CAPRELSA can cause harm to your unborn baby. Tell your healthcare provider if you become pregnant or think you might be pregnant during treatment with CAPRELSA.
  Females who are able to become pregnant:
  - Your healthcare provider must do a pregnancy test before you begin treatment with CAPRELSA.
  - You must use effective birth control (contraception) during your treatment with CAPRELSA and for 4 months after your last dose of CAPRELSA.
  - Talk to your healthcare provider about birth control methods that may be used during treatment with CAPRELSA.
  Males with female partners who are able to become pregnant:
  - You must use effective birth control during treatment with CAPRELSA and for 4 months after your last dose of CAPRELSA.

- are breastfeeding or plan to breastfeed. It is not known if CAPRELSA passes into your breast milk. Do not breastfeed during treatment and for 4 months after your last dose of CAPRELSA.

Tell your healthcare provider about all the medicines you take, including prescription and over-the-counter medicines, vitamins, and herbal supplements. CAPRELSA and other medicines may affect each other causing side effects.
Especially tell your healthcare provider if you take:

- St. John's wort. You should not take St. John's wort during treatment with CAPRELSA
- a medicine for your heart
- bisphosphonate medicines or denosumab

Ask your healthcare provider if you are not sure if your medicine is one listed above.
Do not take other medicines during treatment with CAPRELSA until you have talked with your healthcare provider or pharmacist.
Know the medicines you take. Keep a list of them to show your healthcare provider and pharmacist when you get a new medicine.

How should I take CAPRELSA?

- Take CAPRELSA exactly as your healthcare provider tells you to take it. Do not change your dose or stop taking CAPRELSA unless your healthcare provider tells you to.
- CAPRELSA may be taken with or without food.
- Swallow CAPRELSA tablets whole with water.
- Do not crush CAPRELSA tablets. If CAPRELSA tablets are accidentally crushed, contact with skin should be avoided. If contact occurs, wash affected areas well with water.
- If you cannot swallow CAPRELSA tablets whole:
  - place your dose of CAPRELSA in a glass that contains 2 ounces of noncarbonated water (no other liquids should be used).
  - stir the CAPRELSA tablet(s) and water mixture for about 10 minutes or until the tablet(s) are in very small pieces (the tablets will not completely dissolve).
  - swallow CAPRELSA and water mixture right away.
  - if any CAPRELSA and water mixture remains in the glass, mix with an additional 4 ounces of noncarbonated water and swallow the mixture to make sure that you take your full dose of CAPRELSA.
- If you miss a dose and your next dose is in:
  - less than 12 hours, take your next dose at the normal time. Do not make up for the missed dose.
  - 12 hours or more, take the missed dose as soon as you remember. Take the next dose at the normal time.
- Call your healthcare provider right away if you take too much CAPRELSA.
- Your healthcare provider should check your blood pressure regularly during your treatment with CAPRELSA.

What should I avoid while taking CAPRELSA?

- Limit exposure to the sun. CAPRELSA can make your skin sensitive to the sun. During treatment with CAPRELSA and for at least 4 months after stopping treatment with CAPRELSA, use sun block and wear clothes that cover your skin, including your head, arms, and legs when you go outdoors.
- Use caution before driving or using machinery. Keep in mind CAPRELSA may make you feel tired, or cause blurred vision.

What are the possible side effects of CAPRELSA?
CAPRELSA may cause serious side effects, including:

- See "What is the most important information I should know about CAPRELSA?"
- Severe skin reactions. CAPRELSA can cause severe skin reactions that can lead to death, such as toxic epidermal necrolysis and Stevens-Johnson syndrome, or other serious skin reactions that may affect any part of your body. These severe skin reactions may be life threatening and you may need to be treated in a hospital. Tell your healthcare provider right away if you get any of these symptoms:

- skin rash or acne
- dry skin
- itching
- blisters on your skin
- redness or swelling of your face, hands, or soles of your feet

- blisters or sores in your mouth
- peeling of your skin
- fever
- muscle or joint aches

- Breathing problems (interstitial lung disease). CAPRELSA may cause a breathing problem called interstitial lung disease that can lead to death. Tell your healthcare provider right away if you experience sudden or worsening shortness of breath, cough that does not go away (persistent) or fever.
- Stroke. Strokes have been reported in some people who have taken CAPRELSA and in some cases have caused death. Stop taking CAPRELSA and call your healthcare provider right away if you have symptoms of a stroke which may include:
  - numbness or weakness of the face, arm or leg, especially on one side of the body
  - sudden confusion, trouble speaking or understanding
  - sudden trouble seeing in one or both eyes
  - sudden trouble walking, dizziness, loss of balance or coordination
  - sudden, severe headache
- Bleeding. CAPRELSA can cause serious bleeding that can lead to death. Tell your healthcare provider right away if you have severe bleeding during treatment with CAPRELSA.
- Heart failure. CAPRELSA can cause heart failure that can lead to death. You may have to stop taking CAPRELSA if you have heart failure. Heart failure may not be reversible after stopping CAPRELSA. Your healthcare provider should monitor you for signs and symptoms of heart failure.
- Diarrhea. Diarrhea is common with CAPRELSA and can be severe. Your healthcare provider should check your blood levels to monitor your electrolytes more frequently if you have diarrhea. Tell your healthcare provider if you develop diarrhea during treatment with CAPRELSA.
- Thyroid hormones. You can have changes in your thyroid hormone during treatment with CAPRELSA. Your healthcare provider should monitor your thyroid hormone levels during treatment with CAPRELSA.
- High blood pressure (hypertension). If you develop high blood pressure or your high blood pressure gets worse, your healthcare provider may lower your dose of CAPRELSA or tell you to stop taking CAPRELSA until your blood pressure is under control. Your healthcare provider may prescribe another medicine to control your high blood pressure.
- Reversible Posterior Leukoencephalopathy Syndrome (RPLS). A condition called reversible posterior leukoencephalopathy syndrome can happen while taking CAPRELSA. Call your healthcare provider right away if you get any of these symptoms:

- seizures
- headaches

- changes in vision
- confusion
- problems thinking

- Kidney problems. CAPRELSA may cause problems with your kidneys, including kidney failure.
- Wound healing problems. Wounds may not heal properly during CAPRELSA treatment. Tell your healthcare provider if you plan to have any surgery before starting or during treatment with CAPRELSA.
  - You should stop taking CAPRELSA at least 1 month before planned surgery.
  - Your healthcare provider should tell you when you may start taking CAPRELSA again after surgery.
- Bone problems (osteonecrosis). CAPRELSA may cause death of bone tissue in your jawbone. Your healthcare provider should examine your mouth before you start and during treatment with CAPRELSA. Tell your dentist that you are taking CAPRELSA. It is important for you to practice good mouth care during treatment with CAPRELSA. Tell your healthcare provider right away if you develop any symptoms of jaw problems including jaw pain, toothache, loose teeth or sores on your gums.

The most common side effects of CAPRELSA include:

- rash
- acne
- high blood pressure
- nausea

- headache
- upper respiratory tract infections
- decreased appetite
- stomach-area (abdominal) pain

Tell your healthcare provider if you have any side effect that bothers you or that does not go away.
These are not all of the possible side effects of CAPRELSA. For more information, ask your healthcare provider or pharmacist.
Call your doctor for medical advice about side effects. You may report side effects to FDA at 1-800-FDA-1088.

How should I store CAPRELSA?

- Store CAPRELSA tablets at room temperature between 68°F and 77°F (20°C and 25°C).
- Safely throw away medicine that is out of date or that you no longer need. Ask your pharmacist how to safely throw away CAPRELSA tablets.

Keep CAPRELSA and all medicines out of the reach of children.

General information about the safe and effective use of CAPRELSA.
Medicines are sometimes prescribed for purposes other than those listed in a Medication Guide. Do not use CAPRELSA for a condition for which it was not prescribed. Do not give CAPRELSA to other people, even if they have the same symptoms you have. It may harm them.
You can ask your healthcare provider or pharmacist for information about CAPRELSA that is written for health professionals.

What are the ingredients in CAPRELSA?
Active ingredient: vandetanib
Inactive ingredients:

- Tablet core: calcium hydrogen phosphate dihydrate, crospovidone, magnesium stearate, microcrystalline cellulose, and povidone
- Tablet film-coat: hypromellose 2910, macrogol 300, and titanium dioxide E171

Manufactured for: Genzyme Corporation, Cambridge, MA 02141, A SANOFI COMPANY
CAPRELSA is a registered trademark of Genzyme Corporation.
©2026 Genzyme Corporation.
For more information, go to www.caprelsa.com or call 1-800-633-1610.

This Medication Guide has been approved by the U.S. Food and Drug Administration.

Revised: 1/2026

PRINCIPAL DISPLAY PANEL - 100 mg Tablet Bottle Carton

NDC 58468-7820-3
Rx only

Caprelsa®
(vandetanib) tablets

100 mg

Dispense enclosed medication
guide to each patient.

30 Tablets

PRINCIPAL DISPLAY PANEL - 300 mg Tablet Bottle Carton

NDC 58468-7840-3
Rx only

Caprelsa®
(vandetanib) tablets

300 mg

Dispense enclosed medication
guide to each patient.

30 Tablets